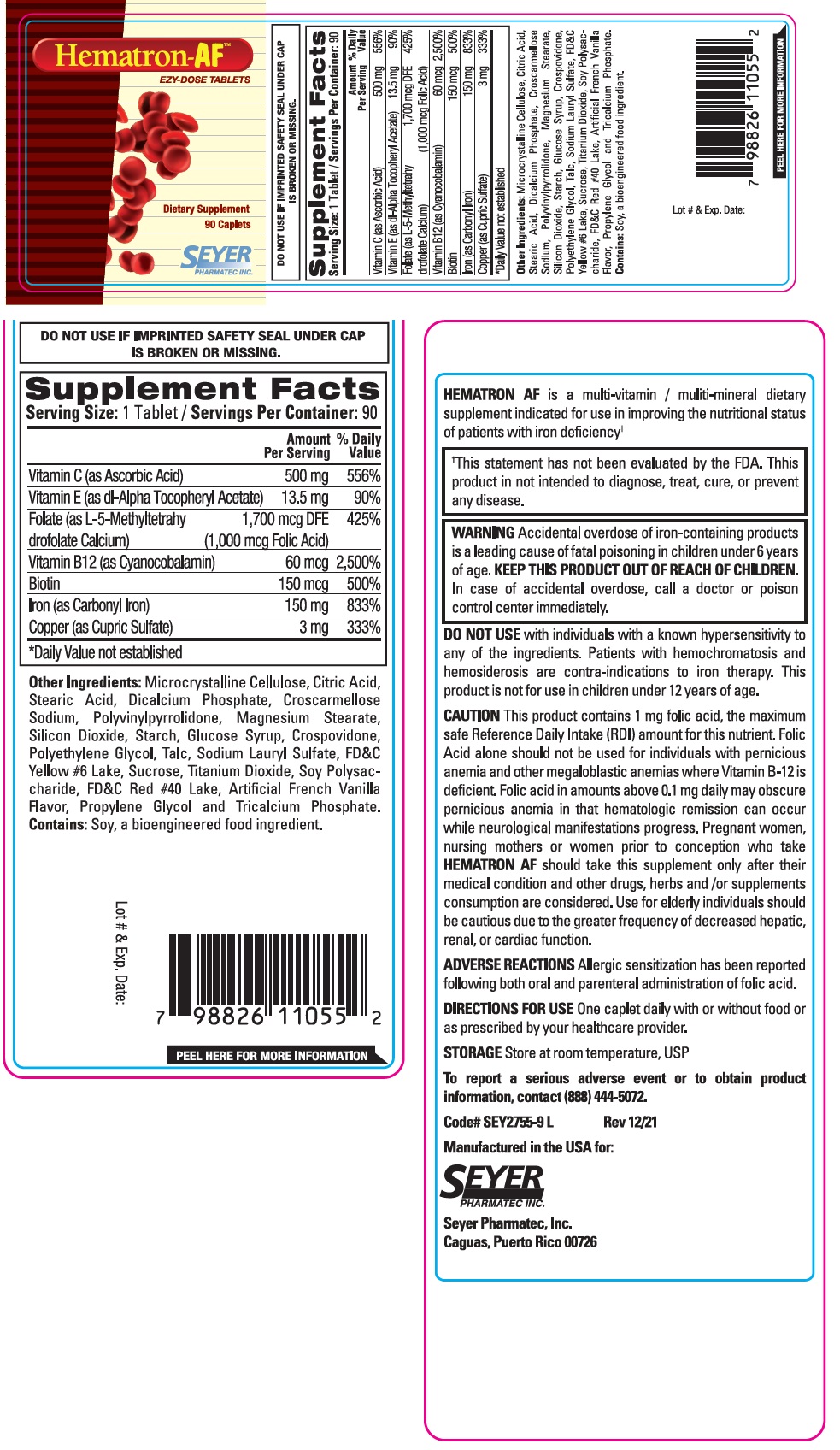 DRUG LABEL: Hematron-AF
NDC: 11026-2760 | Form: TABLET
Manufacturer: Seyer Pharmatec, Inc.
Category: other | Type: DIETARY SUPPLEMENT
Date: 20240814

ACTIVE INGREDIENTS: ASCORBIC ACID 500 mg/1 1; .ALPHA.-TOCOPHEROL ACETATE, DL- 13.5 mg/1 1; LEVOMEFOLATE CALCIUM 1700 ug/1 1; CYANOCOBALAMIN 60 ug/1 1; BIOTIN 150 ug/1 1; IRON 150 mg/1 1; CUPRIC SULFATE 3 mg/1 1
INACTIVE INGREDIENTS: MICROCRYSTALLINE CELLULOSE; CITRIC ACID MONOHYDRATE; STEARIC ACID; ANHYDROUS DIBASIC CALCIUM PHOSPHATE; CROSCARMELLOSE SODIUM; POVIDONE K60; MAGNESIUM STEARATE; SILICON DIOXIDE; STARCH, CORN; CORN SYRUP; CROSPOVIDONE, UNSPECIFIED; POLYETHYLENE GLYCOL, UNSPECIFIED; TALC; SODIUM LAURYL SULFATE; FD&C YELLOW NO. 6; SUCROSE; TITANIUM DIOXIDE; SOYBEAN COTYLEDON CELL WALL POLYSACCHARIDES; FD&C RED NO. 40; PROPYLENE GLYCOL; TRICALCIUM PHOSPHATE

Hematron-AF™

STATEMENT OF IDENTITY

Supplement Facts
Serving Size: 1 Tablet / Servings Per Container: 90
 | Amount | % Daily
 | Per Serving | Value
Vitamin C (as Ascorbic Acid) | 500 mg | 556%
Vitamin E (as dl-Alpha Tocopheryl Acetate) | 13.5 mg | 90%
Folate (as L-5-Methyltetrahydrofolate Calcium) | 1,700 mcg DFE | 425%
 | (1,000 mcg Folic Acid)
Vitamin B12 (as Cyanocobalamin) | 60 mcg | 2,500%
Biotin | 150 mcg | 500%
Iron (as Carbonyl Iron) | 150 mg | 833%
Copper (as Cupric Sulfate) | 3 mg | 333%
*Daily Value not established

Other Ingredients:
Microcrystalline Cellulose, Citric Acid, Stearic Acid, Dicalcium Phosphate, Croscarmellose Sodium, Polyvinylpyrrolidone, Magnesium Stearate, Silicon Dioxide, Starch, Glucose Syrup, Crospovidone, Polyethylene Glycol, Talc, Sodium Lauryl Sulfate, FD&C Yellow #6 Lake, Sucrose, Titanium Dioxide, Soy Polysaccharide, FD&C Red #40 Lake, Artificial French Vanilla Flavor, Propylene Glycol and Tricalcium Phosphate.
Contains: Soy, a bioengineered food ingredient.

HEMATRON AF is a multi-vitamin / multi-mineral dietary supplement indicated for use in improving the nutritional status of patients with iron deficiency†

†This statement has not been evaluated by the FDA. This product is not intended to diagnose, treat, cure, or prevent any disease.

WARNINGS

WARNING Accidental overdose of iron-containing products is a leading cause of fatal poisoning in children under 6 years of age. KEEP THIS PRODUCT OUT OF REACH OF CHILDREN. In case of accidental overdose, call a doctor or poison control center immediately.

DO NOT USE with individuals with a known hypersensitivity to any of the ingredients. Patients with hemochromatosis and hemosiderosis are contra-indications to iron therapy. This product is not for use in children under 12 years of age.

CAUTION

This product contains 1 mg folic acid, the maximum safe Reference Daily Intake (RDI) amount for this nutrient. Folic Acid alone should not be used for individuals with pernicious anemia and other megaloblastic anemias where Vitamin B-12 is deficient. Folic acid in amounts above 0.1 mg daily may obscure pernicious anemia in that hematologic remission can occur while neurological manifestations progress. Pregnant Women, nursing mothers or women prior to conception who take HEMATRON AF should take this supplement only after their medical condition and other drugs, herbs and / or supplements consumption are considered. Use for elderly individuals should be cautious due to the greater frequency of decreased hepatic, renal, or cardiac function.

ADVERSE REACTIONS:
Allergic sensitization has been reported following both oral and parenteral administration of folic acid.

DIRECTIONS FOR USE

One caplet daily with or without food or as prescribed by your healthcare provider.

STORAGE

Store at room temperature, USP.

To report a serious adverse event or to obtain product information, contact (888) 444-5072.

Manufactured in the USA for:
Seyer Pharmatec, Inc.
Caguas, Puerto Rico 00726

DO NOT USE IF IMPRINTED SAFETY SEAL UNDER CAP IS BROKEN OR MISSING.

HEALTH CLAIM

Dietary Supplement

EZY-DOSE TABLETS